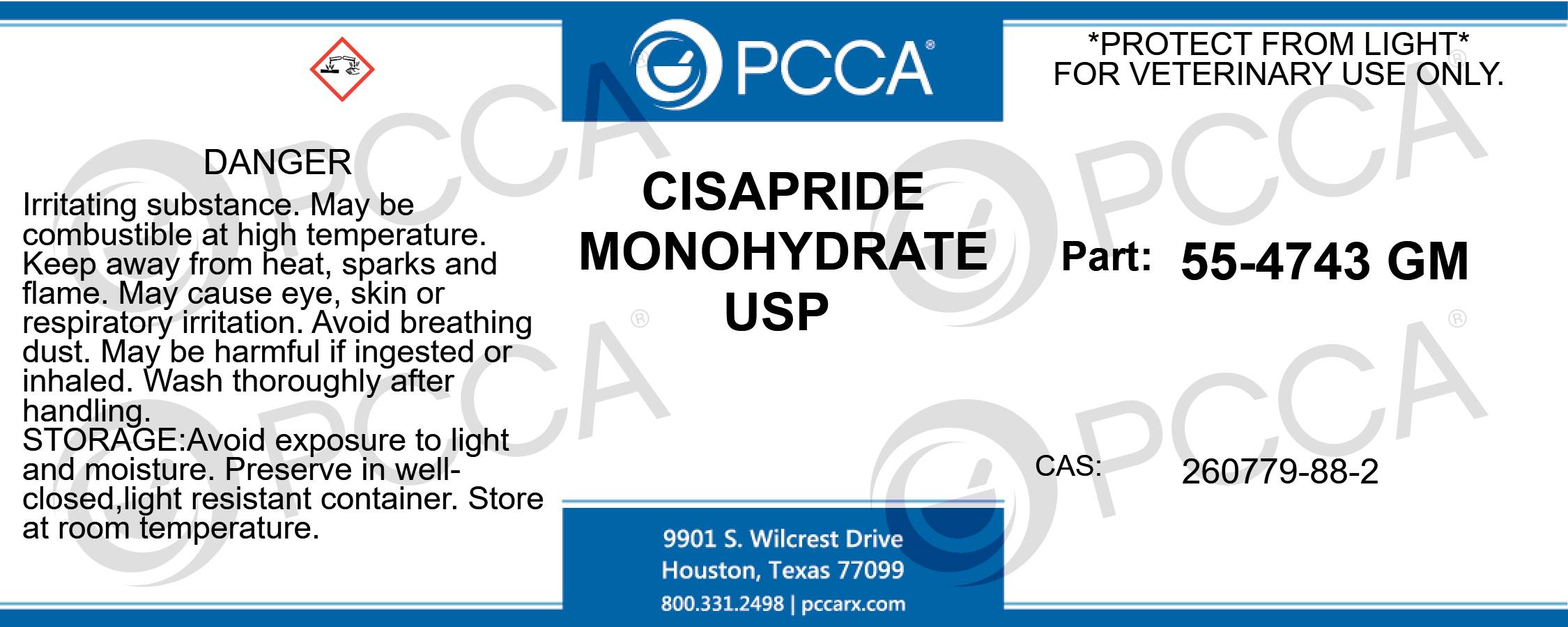 DRUG LABEL: CISAPRIDE MONOHYDRATE
NDC: 51927-0257 | Form: POWDER
Manufacturer: Professional Compounding Centers of America dba PCCA
Category: other | Type: BULK INGREDIENT - ANIMAL DRUG
Date: 20130715

ACTIVE INGREDIENTS: CISAPRIDE MONOHYDRATE 1 kg/1 kg

CISAPRIDE MONOHYDRATE USP

PRINCIPAL DISPLAY PANEL – BULK PRODUCT

CISAPRIDE MONOHYDRATE USP
*PROTECT FROM LIGHT*
FOR VETERINARY USE ONLY.
PART: 55-4743 GM
CAS: 260779-88-2
DANGER: IRRITATING SUBSTANCE. MAY BE COMBUSTIBLE AT HIGH TEMPERATURE. KEEP AWAY FROM HEAT, SPARKS AND FLAME. MAY CAUSE EYE, SKIN OR RESPIRATORY IRRITATION. AVOID BREATHING DUST. MAY BE HARMFUL IF INGESTED OR INHALED. WASH THOROUGHLY AFTER HANDLING. AVOID EXPOSURE TO LIGHT AND MOISTURE. PRESERVE IN WELL-CLOSED,LIGHT RESISTANT CONTAINER. STORE AT ROOM TEMPERATURE.